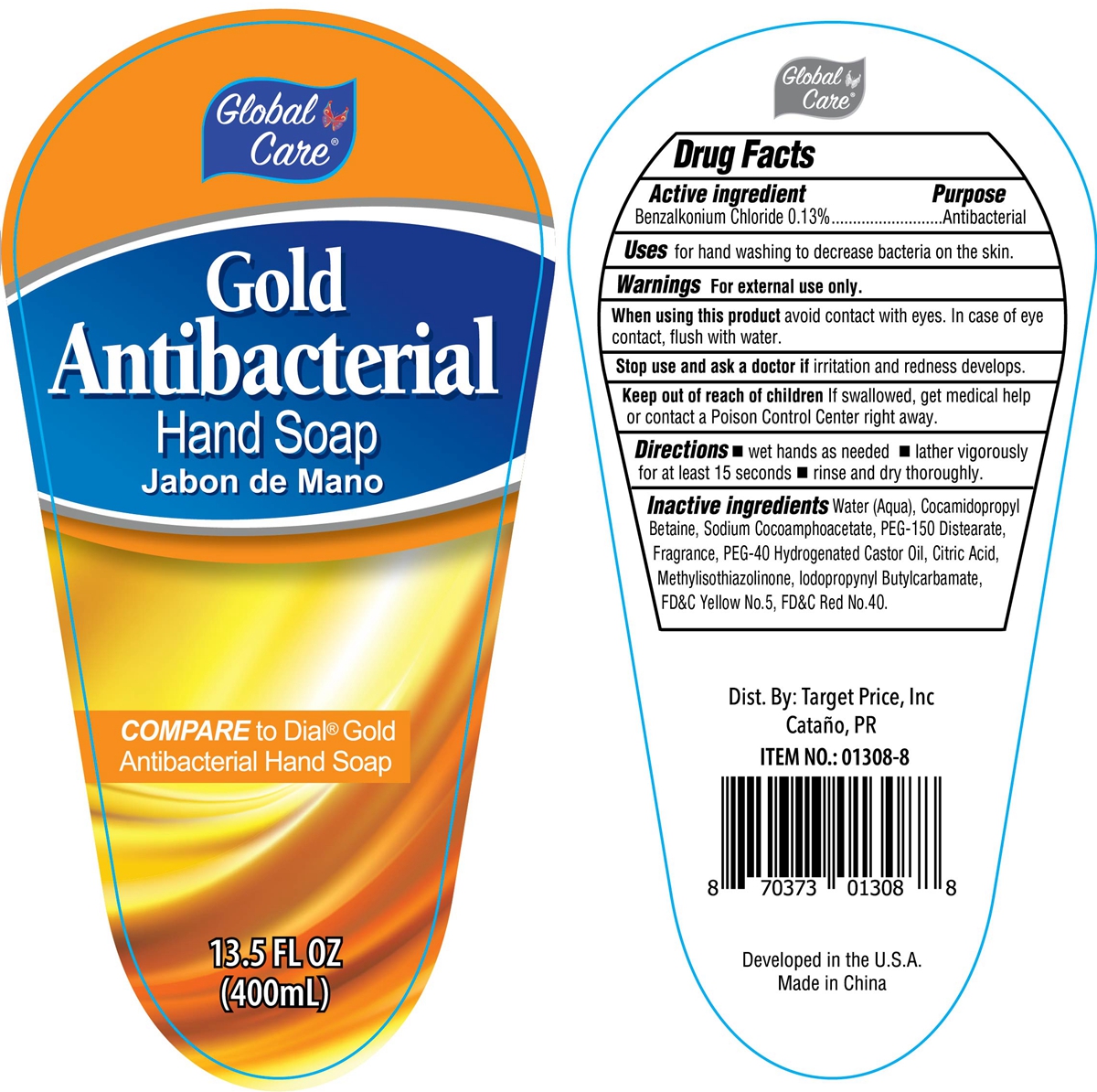 DRUG LABEL: GLOBAL CARE GOLD ANTIBACTERIAL HAND
NDC: 76176-159 | Form: LIQUID
Manufacturer: NINGBO LIYUAN DAILY CHEMICAL PRODUCTS CO., LTD.
Category: otc | Type: HUMAN OTC DRUG LABEL
Date: 20240101

ACTIVE INGREDIENTS: BENZALKONIUM CHLORIDE 0.13 g/100 mL
INACTIVE INGREDIENTS: COCAMIDOPROPYL BETAINE; SODIUM COCOAMPHOACETATE; WATER; IODOPROPYNYL BUTYLCARBAMATE; CITRIC ACID MONOHYDRATE; METHYLISOTHIAZOLINONE; FD&C YELLOW NO. 5; FD&C RED NO. 40; PEG-150 DISTEARATE; HYDROGENATED CASTOR OIL

Purpose

Antibacterial

Uses

for hand washing to decrease bacteria on the skin.

Warnings

For external use only.

When using this product avoid contact with eyes. In case of eye contact, flush with water.

Stop use and ask a doctor if

irritation and redness develops.

Keep out of reach of children.

If swallowed, get medical help or contact a Poison Control Center right away.

Directions

- wet hands as needed
- lather vigorously for at least 15 seconds
- rinse and dry thoroughly.

Inactive ingredients

Water (Aqua), Cocamidopropyl Betaine, Sodium Cocoamphoacetate, PEG-150 Distearate, Fragrance, PEG-40 Hydrogenated Castor Oil, Citric Acid, Methylisothiazolinone, Iodopropynyl Butylcarbamate, FD&C Yellow No. 5, FD&C Red No.40